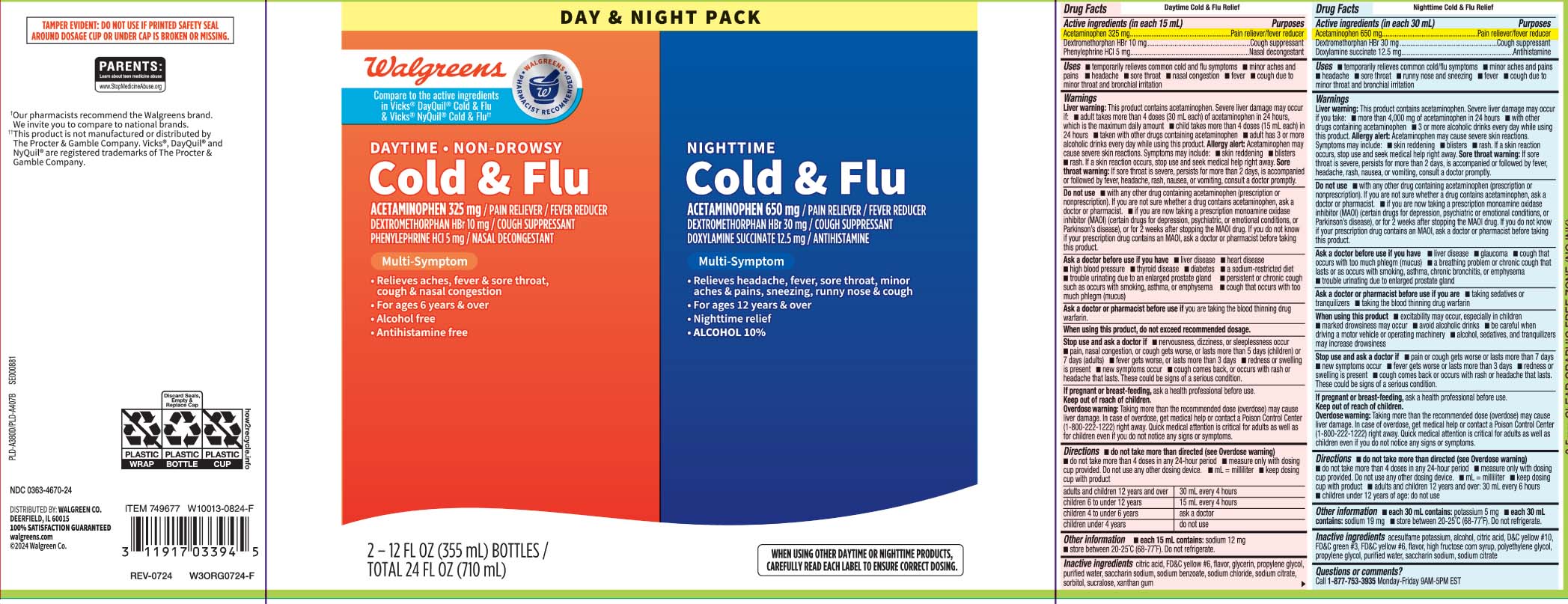 DRUG LABEL: Daytime Nighttime Cold and Cough
NDC: 0363-4670 | Form: KIT | Route: ORAL
Manufacturer: Walgreens
Category: otc | Type: HUMAN OTC DRUG LABEL
Date: 20250908

ACTIVE INGREDIENTS: ACETAMINOPHEN 325 mg/15 mL; DEXTROMETHORPHAN HYDROBROMIDE 10 mg/15 mL; PHENYLEPHRINE HYDROCHLORIDE 5 mg/15 mL; ACETAMINOPHEN 650 mg/30 mL; DEXTROMETHORPHAN HYDROBROMIDE 30 mg/30 mL; DOXYLAMINE SUCCINATE 12.5 mg/30 mL
INACTIVE INGREDIENTS: ANHYDROUS CITRIC ACID; FD&C YELLOW NO. 6; GLYCERIN; PROPYLENE GLYCOL; WATER; SACCHARIN SODIUM; SODIUM BENZOATE; SODIUM CHLORIDE; SORBITOL; SUCRALOSE; XANTHAN GUM; ACESULFAME POTASSIUM; ANHYDROUS CITRIC ACID; ALCOHOL; D&C YELLOW NO. 10; FD&C GREEN NO. 3; FD&C YELLOW NO. 6; PROPYLENE GLYCOL; WATER; TRISODIUM CITRATE DIHYDRATE; HIGH FRUCTOSE CORN SYRUP; POLYETHYLENE GLYCOL, UNSPECIFIED; SACCHARIN SODIUM

Drug Facts

Active ingredients (in each 15 mL) Daytime

Acetaminophen 325 mg

Dextromethorphan HBr 10 mg

Phenylephrine HCl 5 mg

Active ingredients for (in each 30 mL) Nighttime

Acetaminophen 650 mg

Dextromethorphan HBr 30 mg

Doxylamine succinate 12.5 mg

Purposes for Day Time

Pain reliever/Fever reducer

Cough suppressant

Nasal decongestant

Purpose for Night Time

Pain reliever/fever reducer

Cough suppressant

Antihistamine

Uses

DAYTIME

- temporarily relieves common cold and flu symptoms
  - minor aches and pains
  - headache
  - sore throat
  - nasal congestion
  - fever
  - cough due to minor throat and bronchial irritation

NIGHTTIME

- temporarily relieves common cold/flu symptoms
  - minor aches and pain
  - headache
  - sore throat
  - runny nose and sneezing
  - fever
  - cough due to minor throat and bronchial irritations as may occur with a cold

Warnings

DAYTIME NIGHTTIME

Liver warning: This product contain acetaminophen. Severe liver damage may occur if:

- adult takes more than 4 doses (30 mL each) of acetaminophen in 24 hours, which is the maximum daily amount
- child takes more than 4 doses (15 mL each) in 24 hours
- taken with other drugs containing acetaminophen
- adult has 3 or more alcoholic drinks every day while using this product

Allergy alert: Acetaminophen may cause severe skin reactions. Symptoms may include:

- skin reddening
- blisters
- rash.

If a skin reaction occurs, stop use and seek medical help right away.

Sore throat warning: If sore throat is severe, persists for more than 2 days, is accompanied or followed by fever, headache, rash, nausea, or vomiting, consult a doctor promptly.

Do not use

DAYTIME NIGHTTIME

- with any other drug containing acetaminophen (prescription or nonprescription) If you are not sure whether a drug contains acetaminophen, ask a doctor or pharmacist.
- if you are now taking a prescription monoamine oxidase inhibitor (MAOI) (certain drugs for depression, psychiatric, or emotional conditions, or Parkinson's disease), or for 2 weeks after stopping the MAOI drug. If you do not know if your prescription drug contain an MAOI, ask a doctor or pharmacist before taking this product

Ask a doctor before use if have

DAYTIME

- liver disease
- high blood pressure
- heart disease
- thyroid disease
- diabetes
- a sodium-restricted diet
- trouble urinating due to an enlarged prostate gland
- persistent or chronic cough such as occurs with smoking, asthma, or emphysema
- cough that occurs with too much phlegm (mucus)

NIGHTTIME

- liver disease
- glaucoma
- cough that occurs with too much phlegm (mucus)
- trouble urinating due to enlarged prostate gland
- a breathing problem or chronic cough that lasts or occurs with smoking, asthma, chronic bronchitis, or emphysema

Ask a doctor or pharmacist before use if the child is

DAYTIME

if you are taking the blood thinning drug warfarin

NIGHTTIME

- taking sedatives or tranquilizers
- taking the blood thinning drug warfarin

When using this product

DAYTIME

do not exceed recommended dosage.

NIGHTTIME

- excitability may occur, especially in children
- mark drowsiness may occur
- avoid alcoholic drinks
- be careful when driving a motor vehicle or operating machinery
- alcohol, sedatives and tranquilizers may increase drowsiness

Stop use and ask a doctor if

DAYTIME

- nervousness, dizziness or sleeplessness occur
- pain, nasal congestion, or cough gets worse, or lasts more than 5 days (children) or 7 days (adult)
- fever gets worse or lasts more than 3 days
- redness or swelling is present
- new symptoms occur
- cough comes back, or occurs with rash or headache that lasts.persists for more than 7 days, comes back or occurs with a fever, rash or persistent headache.

These could be signs of a serious condition.

NIGHTTIME

- pain or cough gets worse or lasts more than 7 days
- redness or swelling is present
- new symptoms occur
- fever gets worse or lasts more than 3 days
- cough comes back or occurs with rash or headache that lasts

These could be signs of a serious condition.

If pregnant or breast-feeding,

ask a health professional before use.

Keep out of reach of children.

Overdose warning: Taking more than the recommended dose (overdose) may cause liver damage. In case of overdose, get medical help or contact a Poison Control Center (1-800-222-1222) right away. Quick medical attention is critical for adult as well as for children even if you do not notice any signs or symptoms.

Directions

DAYTIME

- do not take more than directed (see Overdose warning)
- do not take more than 4 doses in any 24-hour period
- measure only with dosing cup provided. Do not use any other dosing device.
- keep dosing cup with product
- mL= milliliter

adult and children 12 years and over | 30 mL every 4 hours
children 6 to under 12 years | 15 mL every 4 hours
children 4 to under 6 years | ask a doctor
children under 4 years | do not use

NIGHTTIME

- do not take more than directed (see Overdose warning)
- do not take more than 4 doses in any 24-hour period
- measure only with dosing cup provided. Do not use any other dosing device.
- keep dosing cup with product
- mL= milliliter
- adult and children 12 years and over: 30 mL every 6 hours
- children under 12 years of age: do not use

Other information

DAYTIME

- each 15 mL contains: sodium 12 mg
- store between 20-25ºC (68º-77ºF). Do not refrigerate.

NIGHTTIME

- each 30 mL contains: potassium 5 mg
- each 30 mL contains: sodium 19 mL
- store between 20-25ºC (68-77ºF). Do not refrigerate

Inactive ingredients

DAYTIME

citric acid, FD&C yellow #6, flavor, glycerin, propylene glycol, purified water, saccharin sodium, sodium benzoate, sodium chloride, sodium citrate, sorbitol, sucralose, xanthan gum

NIGHTTIME

acesulfame potassium, alcohol, anhydrous citric acid, D&C yellow #10 FD&C green #3, FD&C yellow #6, flavor, high fructose corn syrup, polyethylene glycol, propylene glycol, purified water, saccharin sodium, trisodium citrate dihydrate

Questions or comments?

Call 1-877-753-3935 Monday-Friday 9AM-5PM EST

Principal Display Panel

Compare to the active ingredients in Vick® Dayquil® Cold & Flu & Vick® Nyquil® Cold & Flu††

DAYTIME • NON-DROWSY

Cold & Cough

ACETAMINOPHEN 325 mg / PAIN RELIEVER / FEVER REDUCER

DEXTROMETHORPHAN HBr 10 mg / COUGH SUPPRESSANT

PHENYLEPHRINE HCI 5 mg / NASAL DECONGESTANT

Multi-Symptom

- Relieves aches, fever,& sore throat, cough & nasal congestion
- For ages 6 years & over
- Alcohol free
- Antihistamine free

FL OZ (mL)

NIGHTTIME

Cold & Flu

ACETAMINOPHEN 650 mg / PAIN RELIEVER / FEVER REDUCER

DEXTROMETHORPHAN HBr 30 mg / COUGH SUPPRESSANT

DOXYLAMINE SUCCINATE 12.5 mg / ANTIHISTAMINE

Multi-Symptom

- Relieves headache, fever, sore throat, minor aches & pains, sneezing, runny nose & cough
- For ages 12 years & over
- Nighttime relief
- ALCOHOL 10%

FL OZ (mL)

WHEN USING OTHER DAYTIME OR NIGHTTIME PRODUCTS, CAREFULLY READ EACH LABEL TO ENSURE CORRECT DOSING

TAMPER EVIDENT: DO NOT USE IF PRINTED SAFETY SEAL AROUND DOSAGE CUP OR UNDER CAP IS BROKEN OR MISSING

KEEP OUTER CARTON FOR COMPLETE WARNINGS AND PRODUCT INFORMATION

††These products are not manufactured or distributed by The Procter & Gamble Company. Vicks®, DayQuil® and Nyquil® are registered trademarks of the Procter & Gamble Company.

DISTRIBUTED BY: WALGREEN CO.

200 WILMOT RD., DEERFIELD, IL 60015 walgreens.com

Product Label

WALGREENS Daytime Nighttime Cold and Flu